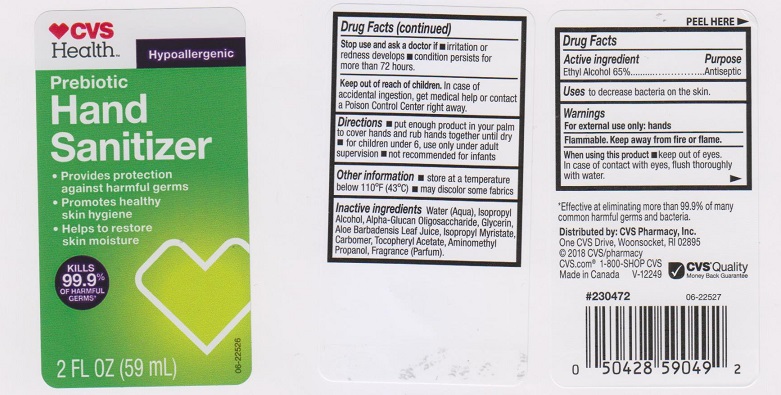 DRUG LABEL: CVS Health Prebiotic Sanitizer
NDC: 59779-778 | Form: LIQUID
Manufacturer: CVS Pharmacy
Category: otc | Type: HUMAN OTC DRUG LABEL
Date: 20180201

ACTIVE INGREDIENTS: ALCOHOL 650 mg/1 mL
INACTIVE INGREDIENTS: WATER; ISOPROPYL ALCOHOL; .ALPHA.-GLUCAN OLIGOSACCHARIDE; GLYCERIN; ALOE VERA LEAF; ISOPROPYL MYRISTATE; CARBOMER 934; .ALPHA.-TOCOPHEROL ACETATE, DL-; AMINOMETHYLPROPANOL

Drug Facts

Active ingredient

Ethyl Alcohol 65%

Purpose

Antiseptic

Uses

to decrease bacteria on the skin.

Warnings

For external use only: hands

Flammable. Keep away from fire or flame.

When using this product

keep out of eyes. In case of contact with eyes, flush thoroughly with water.

Stop use and ask a doctor if

- irritation or redness develops
- condition persists for more than 72 hours

Keep out of reach of children.

In case of accidental ingestion, get medical help or contact a Poison Control Center right away.

Directions

- put enough product in your palm to cover hands and rub hands together until dry
- for children under 6, use lonly under adult supervision
- not recommended for infants

Other information

- store at atemperature below 110°F (43°C)
- may discolor some fabrics

Inactive ingredients

Water (Aqua), Isopropyl Alcohol, Alpha-Glucan Oligosaccharide, Glycerin, Aloe Barbadensis Leaf Juice, Isopropyl Myristate, Carbomer, Tocopheryl Acetate, Aminomethyl Propanol, Fragrance (Parfum).